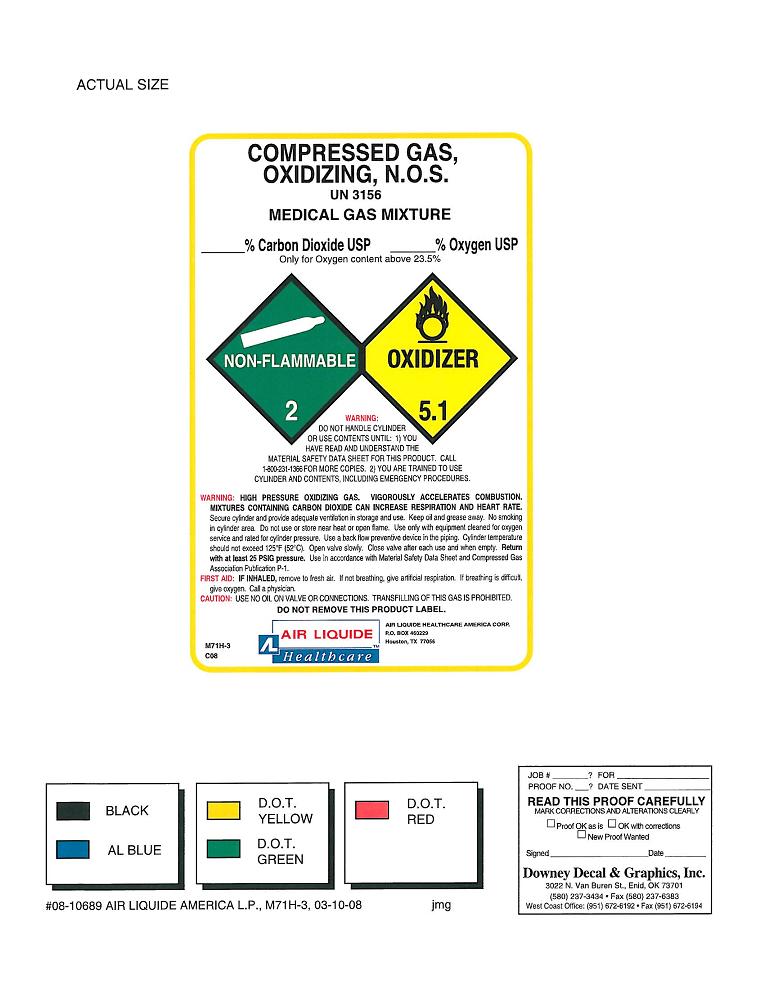 DRUG LABEL: Carbon Dioxide Oxygen Mixture
NDC: 64735-060 | Form: GAS
Manufacturer: Air Liquide Healthcare America Corporation
Category: prescription | Type: HUMAN PRESCRIPTION DRUG LABEL
Date: 20100625

ACTIVE INGREDIENTS: Oxygen 95 L/100 L; Carbon Dioxide 5 L/100 L

CARBON DIOXIDE OXYGEN MIXTURE COMPRESSED

PACKAGE LABEL

Enter section text here

WARNINGS AND PRECAUTIONS

Enter section text here

WARNING: DO NOT HANDLE CYLINDER OR USE CONTENTS UNTIL: 1) YOU HAVE READ AND UNDERSTAND THE MATERIAL SAFETY DATA SHEET FOR THIS PRODUCT. CALL 1-800-231-1366 FOR MORE COPIES. 2) YOU ARE TRAINED TO USE CYLINDER AND CONTENTS, INCLUDING EMERGENCY PROCEDURES.
WARNING: HIGH PRESSURE OXIDIZING GAS. VIGOROUSLY ACCELERATES COMBUSTION. MIXTURES CONTAINING CARBON DIOXIDE CAN INCREASE RESPIRATION AND HEART RATE. Secure Cylinder and provide adequate ventilation in storage and use. Keep oil and grease away. No smoking in cylinder area. Do not use or store near heat or open flame. Use only with equipment cleaned for oxygen service and rated for cylinder pressure. Use a back flow preventive device in the piping. Cylinder temperature should not exceed 125°F (52°C). Open valve slowly. Close valve after each use and when empty. Return with at least 25 PSIG pressure. Use in accordance with Material Safety Data Sheet and Compressed Gas Association Publication P-1.
FIRST AID: IF INHALED, remove to fresh air. If not breathing, give artificial respiration. If breathing is difficult, give oxygen. Call a physician.
CAUTION: USE NO OIL ON VALVE OR CONNECTIONS. TRANSFILLING OF THIS GAS IS PROHIBITED.
DO NOT REMOVE THIS PRODUCT LABEL.